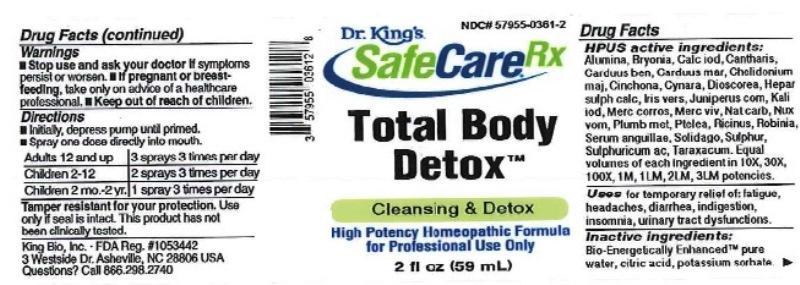 DRUG LABEL: Total Body Detox
NDC: 57955-0361 | Form: LIQUID
Manufacturer: King Bio Inc.
Category: homeopathic | Type: HUMAN OTC DRUG LABEL
Date: 20161205

ACTIVE INGREDIENTS: ALUMINUM OXIDE 10 [hp_X]/59 mL; BRYONIA ALBA ROOT 10 [hp_X]/59 mL; CALCIUM IODIDE 10 [hp_X]/59 mL; LYTTA VESICATORIA 10 [hp_X]/59 mL; CENTAUREA BENEDICTA 10 [hp_X]/59 mL; MILK THISTLE 10 [hp_X]/59 mL; CHELIDONIUM MAJUS 10 [hp_X]/59 mL; CINCHONA OFFICINALIS BARK 10 [hp_X]/59 mL; CYNARA SCOLYMUS LEAF 10 [hp_X]/59 mL; DIOSCOREA VILLOSA TUBER 10 [hp_X]/59 mL; CALCIUM SULFIDE 10 [hp_X]/59 mL; IRIS VERSICOLOR ROOT 10 [hp_X]/59 mL; JUNIPER BERRY 10 [hp_X]/59 mL; POTASSIUM IODIDE 10 [hp_X]/59 mL; MERCURIC CHLORIDE 10 [hp_X]/59 mL; MERCURY 10 [hp_X]/59 mL; SODIUM CARBONATE 10 [hp_X]/59 mL; STRYCHNOS NUX-VOMICA SEED 10 [hp_X]/59 mL; LEAD 10 [hp_X]/59 mL; PTELEA TRIFOLIATA BARK 10 [hp_X]/59 mL; RICINUS COMMUNIS SEED 10 [hp_X]/59 mL; ROBINIA PSEUDOACACIA BARK 10 [hp_X]/59 mL; ANGUILLA ROSTRATA BLOOD SERUM 10 [hp_X]/59 mL; SOLIDAGO VIRGAUREA FLOWERING TOP 10 [hp_X]/59 mL; SULFUR 10 [hp_X]/59 mL; SULFURIC ACID 10 [hp_X]/59 mL; TARAXACUM OFFICINALE 10 [hp_X]/59 mL
INACTIVE INGREDIENTS: WATER; ANHYDROUS CITRIC ACID; POTASSIUM SORBATE

Total Body Detox™

ACTIVE INGREDIENT

Drug Facts__________________________________________________________________________________________________________

HPUS active ingredients: Alumina, Bryonia alba, Calcarea iodata, Cantharis, Carduus benedictus, Carduus marianus, Chelidonium majus, Cinchona officinalis, Cynara scolymus, Dioscorea villosa, Hepar sulphuris calcareum, Iris versicolor, Juniperus communis, Kali iodatum, Mercurius corrosivus, Mercurius vivus, Natrum carbonicum, Nux vomica, Plumbum metallicum, Ptelea trifoliata, Ricinus communis, Robinia pseudoacacia, Serum anguillae, Solidago virgaurea, Sulphur, Sulphuricum acidum, Taraxacum officinale. Equal volumes of each ingredient in 10X, 30X, 100X, 1M, 1LM, 2LM, 3LM potencies.

INDICATIONS AND USAGE

Uses for temporary relief of: fatigue, headaches, diarrhea, indigestion, insomnia, urinary tract dysfunctions.

Inactive Ingredients:

Bio-Energetically Enhanced™ pure water, citric acid and potassium sorbate.

Warnings

- Stop use and ask your doctor if symptoms persist or worsen.
- If pregnant or breast-feeding, take only on advice of a healthcare professional.

- Keep out of reach of children.

Directions

- Initially, depress pump until primed.
- Spray one dose directly into mouth.
- Adults 12 and up: 3 sprays 3 times per day
- Children 2-12: 2 sprays 3 times per day
- Children 2mo-2yr.: 1 spray 3 times per day

OTHER SAFETY INFORMATION

Tamper resistant for your protection. Use only if safety seal is intact. This product has not been clinically tested.

PURPOSE

Uses for temporary relief of:

- fatigue
- headaches
- diarrhea
- indigestion
- insomnia
- urinary tract dysfunctions